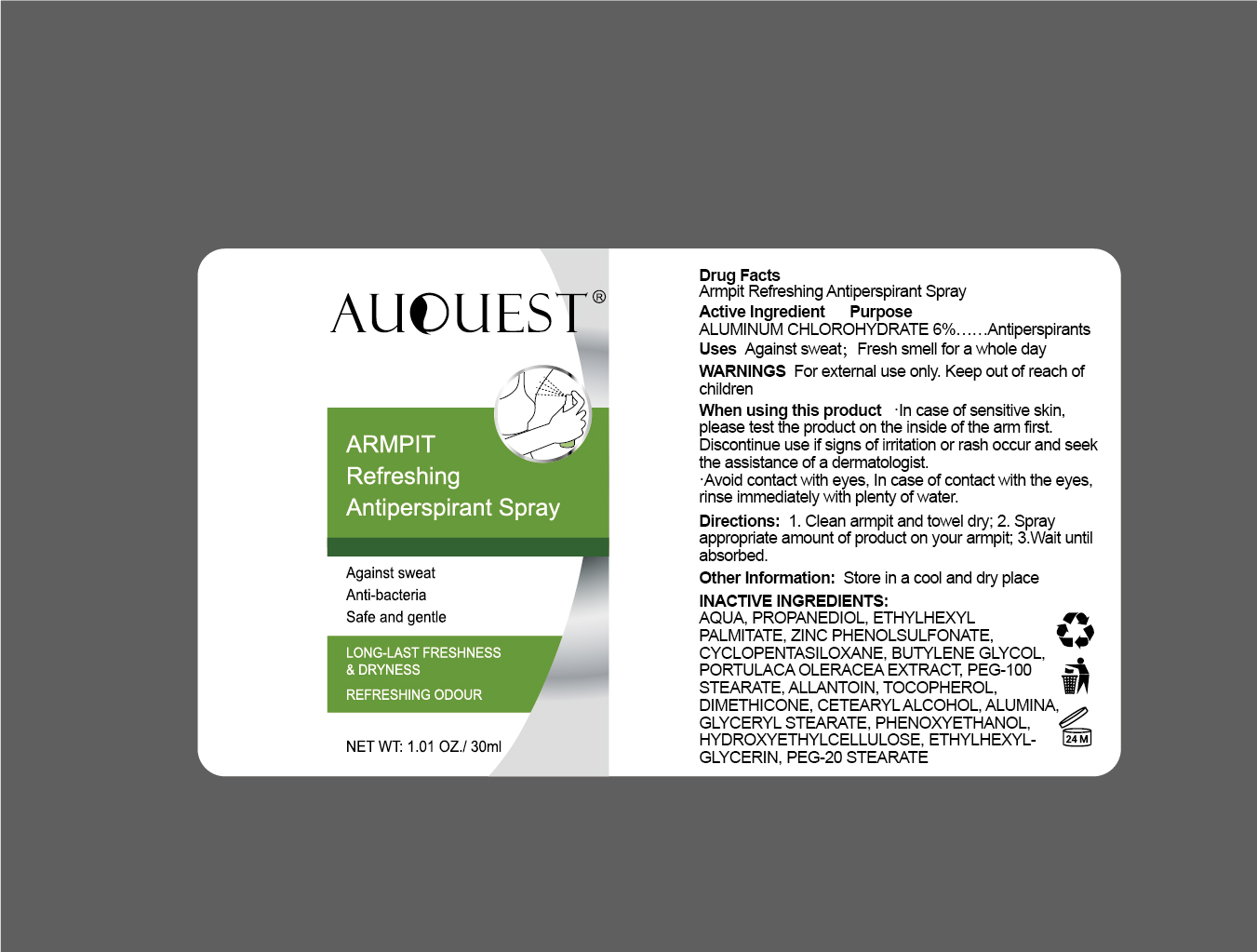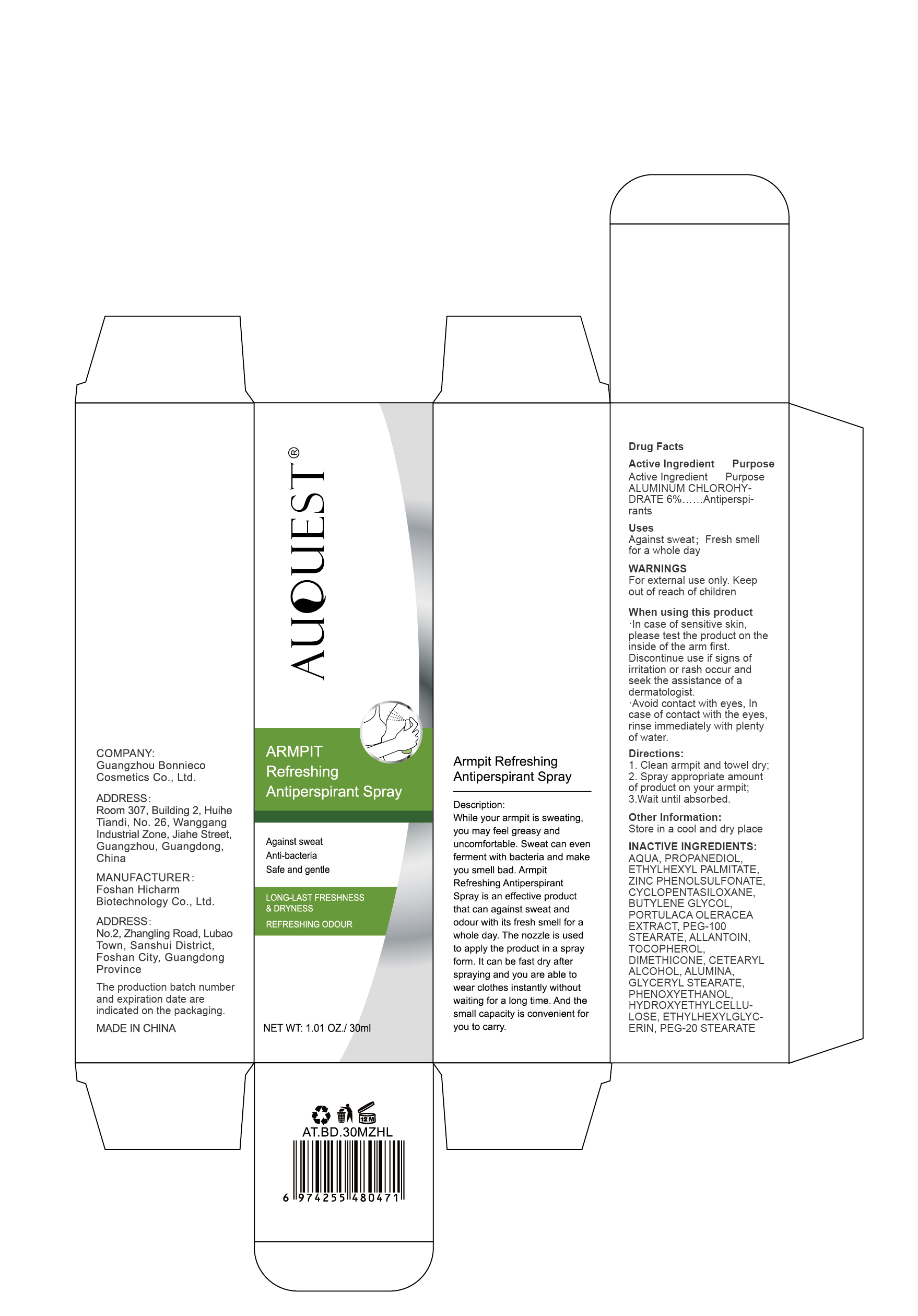 DRUG LABEL: AuQuest ARMPIT Refreshing  Antiperspirant Spray.
NDC: 84186-010 | Form: SPRAY
Manufacturer: Guangzhou Bonnieco Cosmetics Co., Ltd
Category: otc | Type: HUMAN OTC DRUG LABEL
Date: 20240401

ACTIVE INGREDIENTS: ALUMINUM CHLOROHYDRATE 6 g/100 mL
INACTIVE INGREDIENTS: CETOSTEARYL ALCOHOL; ALUMINUM OXIDE; HYDROXYETHYL CELLULOSE, UNSPECIFIED; ETHYLHEXYLGLYCERIN; BUTYLENE GLYCOL; TOCOPHEROL; CYCLOMETHICONE 5; ALLANTOIN; WATER; ETHYLHEXYL PALMITATE; DIMETHICONE; PROPANEDIOL; PURSLANE; POLYOXYL 100 STEARATE; PHENOXYETHANOL; ZINC PHENOLSULFONATE; GLYCERYL MONOSTEARATE; PEG-20 STEARATE

84186-010

Active Ingredient

ALUMINUM CHLOROHYDRATE 6%

Purpose

Deodorant, Antiperspirant

Use

Against sweat;Fresh smellfor a whole day

Warnings

For external use only. Keepout of reach of children

Do not use

ln case of sensitive skin,-ln case of sensitive skin,-ln case of sensitive skin,-Avoid contact with eyes,Incase of contact with the eyes,rinse immediately with plentyof water.Avoid contact with eyes,Incase of contact with the eyes,rinse immediately with plentyof water.

Stop Use

If discomfort arises, please immediately stop using the product and seek the assistance of a dermatologist.

Ask Doctor

If discomfort arises, please immediately stop using the product and seek the assistance of a dermatologist.

Keep Oot Of Reach Of Children

Keep out of reach of children. If swallowed call emergency services.

Directions

1.Clean armpit and towel dry;
2.Spray appropriate amount ofproduct on your armpit
3.Wait until absorbed.

Other information

Store in a cool and dry place

Inactive ingredients

AQUA, PROPANEDIOL, ETHYLHEXYL PALMITATE, ZINC PHENOLSULFONATE, CYCLOPENTASILOXANE, BUTYLENE GLYCOL, PORTULACA OLERACEA EXTRACT, PEG-100 STEARATE, ALLANTOIN, TOCOPHEROL, DIMETHICONE, CETEARYL ALCOHOL, ALUMINA, GLYCERYL STEARATE, PHENOXYETHANOL, HYDROXYETHYLCELLULOSE, ETHYLHEXYLGLYCERIN, PEG-20 STEARATE